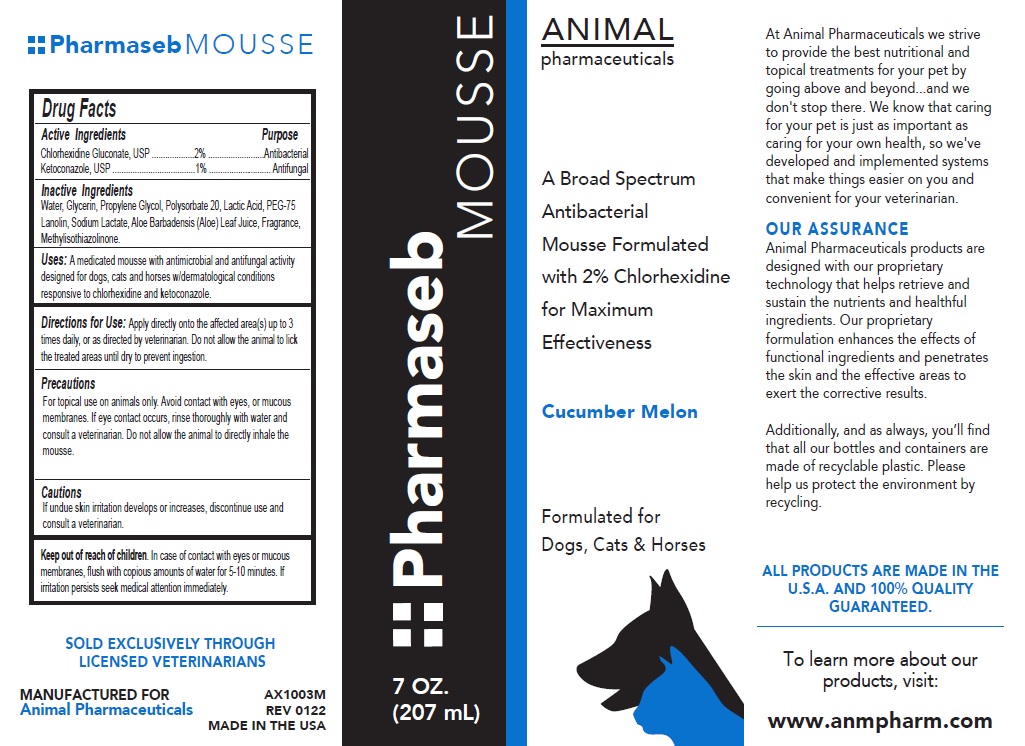 DRUG LABEL: Pharmaseb MOUSSE - Cucumber Melon
NDC: 68898-128 | Form: SOLUTION
Manufacturer: Animal Pharmaceuticals
Category: animal | Type: OTC ANIMAL DRUG LABEL
Date: 20221121

ACTIVE INGREDIENTS: CHLORHEXIDINE GLUCONATE 2 g/100 mL; KETOCONAZOLE 1 g/100 mL
INACTIVE INGREDIENTS: WATER; GLYCERIN; PROPYLENE GLYCOL; POLYSORBATE 20; LACTIC ACID, UNSPECIFIED FORM; PEG-75 LANOLIN; SODIUM LACTATE; ALOE VERA LEAF; METHYLISOTHIAZOLINONE

Pharmaseb MOUSSE Cucumber Melon

Active Ingredients

Chlorhexidine Gluconate, USP ........2%
Ketoconazole, USP ..........................1%

Purpose

Antibacterial
Antifungal

Inactive Ingredients

Water, Glycerin, Propylene Glycol, Polysorbate 20, Lactic Acid, PEG-75 Lanolin, Sodium Lactate, Aloe Barbadensis (Aloe) Leaf Juice, Fragrance, Methylisothiazolinone.

Uses:

A medicated mousse with antimicrobial and antifungal activity designed for dogs, cats and horses w/dermatological conditions responsive to chlorhexidine and ketoconazole.

Directions for Use:

Apply directly onto the affected area(s) up to 3 times daily, or as directed by veterinarian. Do not allow the animal to lick the treated areas until dry to prevent ingestion.

Precautions

For topical use on animals only. Avoid contact with eyes, or mucous membranes. If eye contact occurs, rinse thoroughly with water and consult a veterinarian. Do not allow the animal to directly inhale the mousse.

Cautions

If undue skin irritation develops or increases, discontinue use and consult a veterinarian.

Keep out of reach of children. In case of contact with eyes or mucous membranes, flush with copious amounts of water for 5-10 minutes. If irritation persists seek medical attention immediately.

A Broad Spectrum Antibacterial Mousse Formulated with 2% Chlorhexidine for Maximum Effectiveness

Formulated for Dogs, Cats & Horses

At Animal Pharmaceuticals we strive to provide the best nutritional and topical treatments for your pet by going above and beyond.... and we don't stop there. We know that caring for your pet is just as important as caring for your own health, so we've developed and implemented systems that make things easier on you and convenient for your veterinarian.

OUR ASSURANCE
Animal Pharmaceuticals products are designed with our proprietary technology that helps retrieve and sustain the nutrients and healthful ingredients. Our proprietary formulation enhances the effects of functional ingredients and penetrates the skin and the effective areas to exert the corrective results.

Additionally, and as always, you'll find that all our bottles and containers are made of recyclable plastic. Please help us protect the environment by recycling.

ALL PRODUCTS ARE MADE IN THE U.S.A. AND 100% QUALITY GUARANTEED.

To learn more about our products, visit:
www.anmpharm.com

SOLD EXCLUSIVELY THROUGH LICENSED VETERINARIANS

MANUFACTURED FOR
Animal Pharmaceuticals

MADE IN THE USA